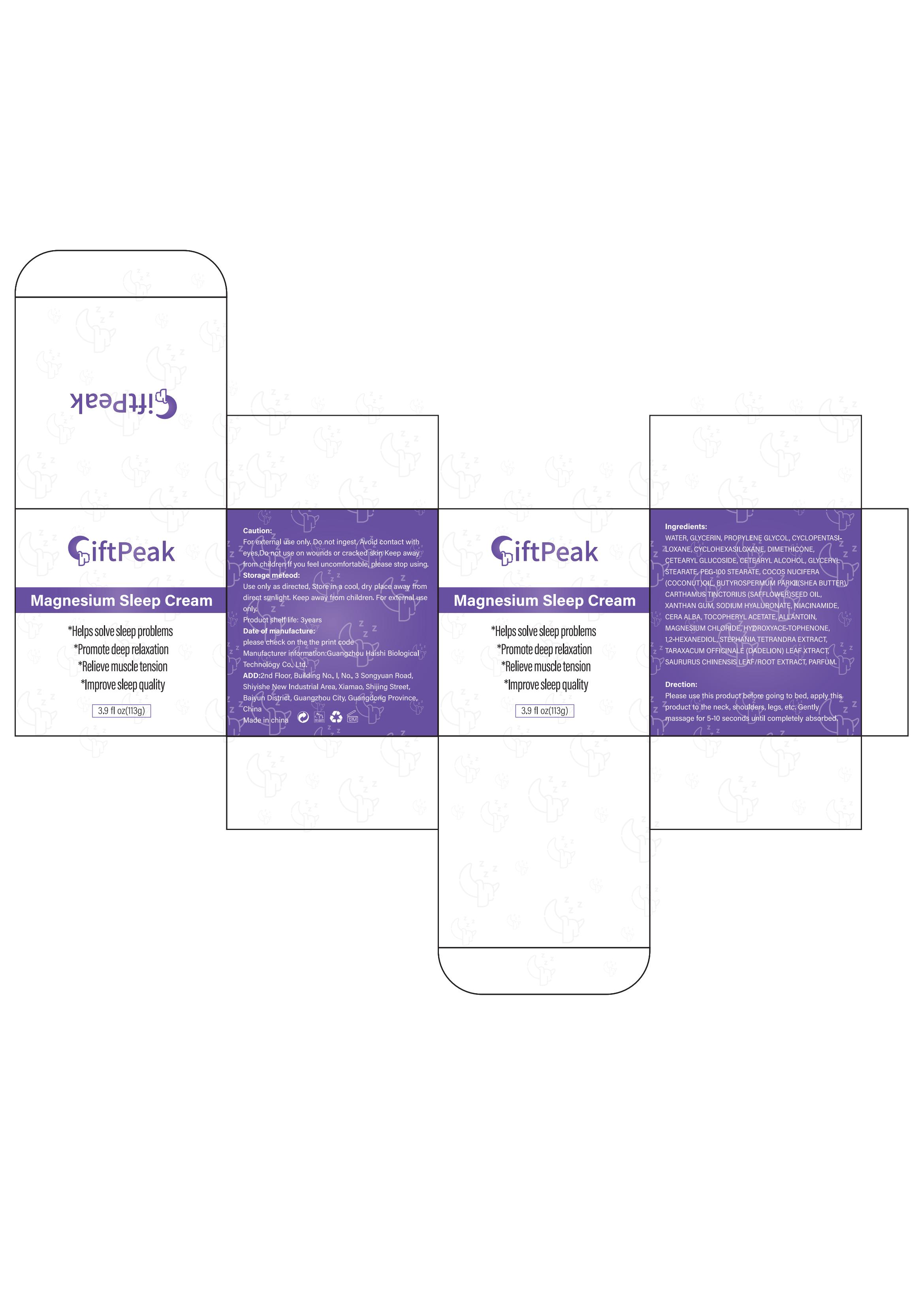 DRUG LABEL: Giftpeak Magnesium Sleep Cream
NDC: 60771-0003 | Form: CREAM
Manufacturer: Guangzhou Haishi Biological Technology Co., Ltd.
Category: otc | Type: HUMAN OTC DRUG LABEL
Date: 20241009

ACTIVE INGREDIENTS: TARAXACUM OFFICINALE LEAF 0.5 g/100 g; NIACINAMIDE 0.5 g/100 g; COCONUT OIL 1 g/100 g; SAFFLOWER OIL 1 g/100 g; DIMECROTATE MAGNESIUM 1 g/100 g
INACTIVE INGREDIENTS: GLYCERIN; DIPROPYLENE GLYCOL

Giftpeak Magnesium Sleep Cream

Warnings

For external use only.

Stop use and ask a doctor if

rash occurs.

Do not use

on damaged or broken skin.

When using this product

keep out of eyes. Rinse with water to remove.

Keep out of reach of children.

If swallowed, get medical help or contact a Poison Control Center right away.

Purpose

*Helps solve sleep problems
*Promote deep relaxation
*Relieve muscle tension*lmprove sleep quality

Uses

Please use this product before going to bed, apply thisproduct to the neck, shoulders, legs, etc, Gentlymassage for 5-10 seconds until completely absorbed,

Active ingredients

COCOS NUCIFERA (COCONUT) OIL 1%
CARTHAMUS TINCTORIUS (SAFFLOWER) SEED OIL 1%
NIACINAMIDE 0.5%
MAGNESIUM CHLORIDE 1%
TARAXACUM OFFICINALE (DANDELION) LEAF EXTRACT 0.5%

Dosage

Apply an appropriate amount of magnesium cream to the desired location.

Inactive ingredients

TOCOPHERYL ACETATE 0.5%

SODIUM HYALURONATE 0.1%

BUTYROSPERMUM PARKII (SHEA BUTTER)1%
STEPHANIA TETRANDRA EXTRACT 0.5%
SAURURUS CHINENSIS LEAF/ROOT EXTRACT 0.5%

WATER 70.35%
GLYCERIN 6%
PROPYLENE GLYCOL 4%
CYCLOPENTASILOXANE 1.4%
CYCLOHEXASILOXANE 0.6%
DIMETHICONE 2%
CETEARYL GLUCOSIDE 2%
CETEARYL ALCOHOL 3%
GLYCERYL STEARATE 1%
PEG-100 STEARATE 1%
XANTHAN GUM 0.4%
CERA ALBA 0.5%
ALLANTOIN 0.1%
HYDROXYACETOPHENONE 0.5%
1,2-HEXANEDIOL 0.5%
PARFUM 0.05%